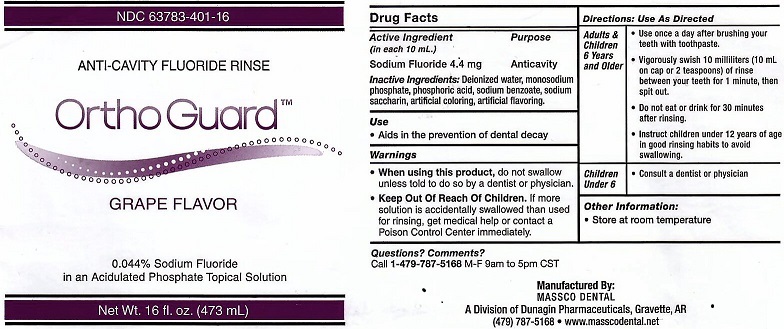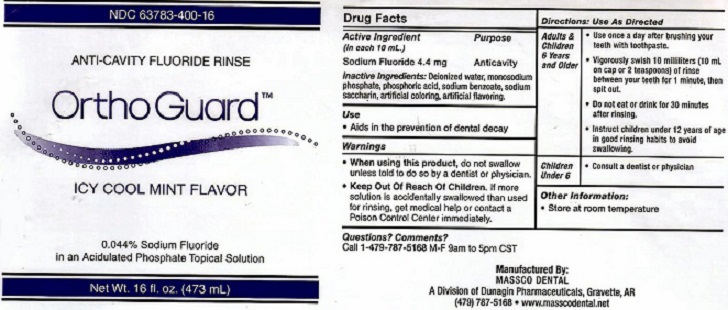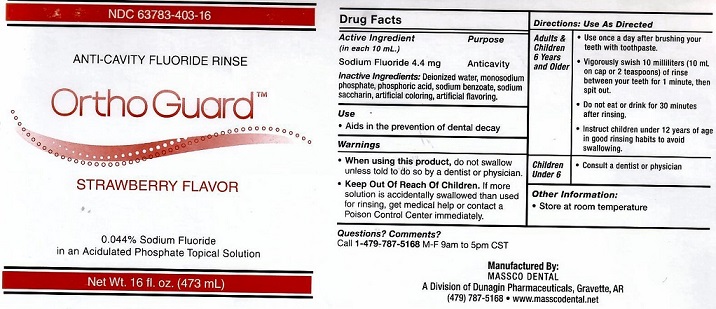 DRUG LABEL: ORTHO GUARD
NDC: 63783-400 | Form: GEL, DENTIFRICE
Manufacturer: Massco Dental A Division of Dunagin Pharmaceuticals
Category: otc | Type: HUMAN OTC DRUG LABEL
Date: 20231217

ACTIVE INGREDIENTS: SODIUM FLUORIDE 4.4 mg/10 mL
INACTIVE INGREDIENTS: SODIUM PHOSPHATE, MONOBASIC, MONOHYDRATE; SODIUM BENZOATE; SACCHARIN SODIUM

ACTIVE INGREDIENT (IN EACH 10 ml)

SODIUM FLUORIDE 4.4 mg

Purpose

Anticavity

Inactive Ingredients: Deionized water, monosodium

phosphate, phosphoric acid, sodium benzoate, sodium

saccharin, artificial coloring, artificial flavoring.

Use

Aids in the prevention of dental decay

Warnings

- When using this product, do not swallow unless to do so by a dentist or physician.

- If more solution is accidentally swallowed than used for rinsing, get medical help or
- contact a Poison Control Center immediately.

KEEP OUT OF REACH OF CHILDREN

DOSAGE AND ADMINISTRATION

DIRECTIONS: Use As Directed

ADULTS AND CHILDREN 6 YEARS AND OLDER

USE ONCE A DAY AFTER BRUSHING YOUR TEETH WITH TOOTHPASTE. VIGOROUSLY SWISH 10 MILLILITERS (10 ml ON CAP OR 2 TEASPOONS) OF RINSE BETWEEN YOUR TEETH FOR 1 MINUTE THEN SPIT OUT. DO NOT EAT OR DRINK FOR 30 MINUTES AFTER RINSING. INSTRUCT CHILDREN UNDER 12 YEARS OF AGE IN GOOD RINSING HABITS TO AVOID SWALLOWING.

CHILDREN UNDER 6

CONSULT A DENTIST OR PHYSICIAN

OTHER INFORMATION

- Store at room temperature.

QUESTIONS? COMMENTS?

CALL 1-479-787-5168 M-F 9 am TO 5pm CST

PACKAGE LABEL

ORTHOGUARD ANTI-CAVITY FLUORIDE RINSE 0.044% SODIUM FLUORIDE IN AN ACIDULATED PHOSPHATE TOPICAL SOLUTION. MANUFACTURED BY MASSCO DENTAL A DIVISION OF DUNAGIN PHARMACEUTICALS, GRAVETTE AR (479) 787-5168. WWW.MASSCODENTAL.NET

res